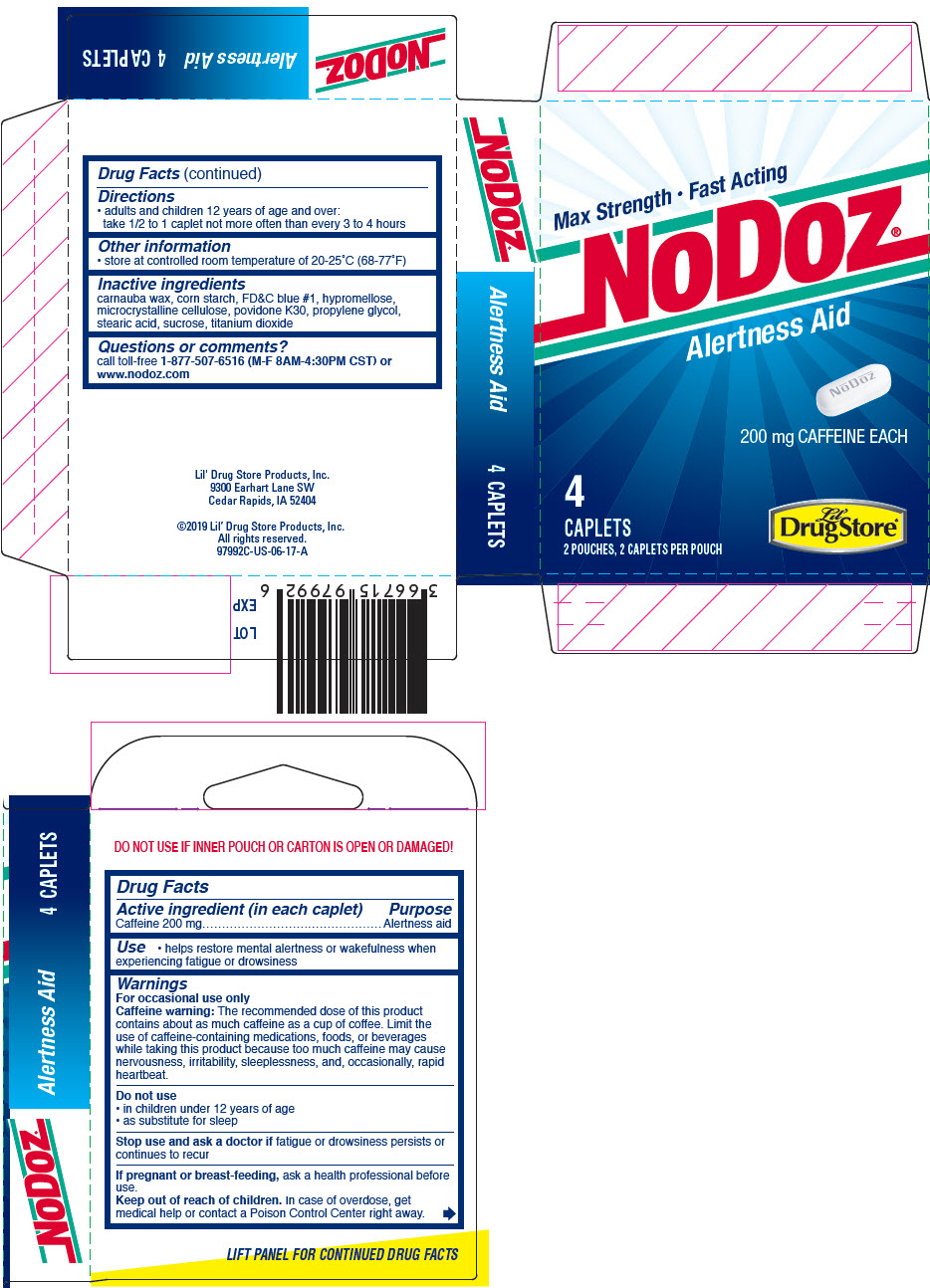 DRUG LABEL: NoDoz Alertness Aid
NDC: 66715-9799 | Form: TABLET, FILM COATED
Manufacturer: Lil' Drug Store Products, Inc.
Category: otc | Type: HUMAN OTC DRUG LABEL
Date: 20220420

ACTIVE INGREDIENTS: CAFFEINE 200 mg/1 1
INACTIVE INGREDIENTS: CARNAUBA WAX; STARCH, CORN; FD&C BLUE NO. 1; HYPROMELLOSE, UNSPECIFIED; MICROCRYSTALLINE CELLULOSE; POVIDONE, UNSPECIFIED; PROPYLENE GLYCOL; STEARIC ACID; SUCROSE; TITANIUM DIOXIDE

NoDoz® Alertness Aid
Maximum Strength

Drug Facts

Active ingredient (in each caplet)

Caffeine 200 mg

Purpose

Alertness aid

Use

- helps restore mental alertness or wakefulness when experiencing fatigue or drowsiness

Warnings

For occasional use only

Caffeine warning

The recommended dose of this product contains about as much caffeine as a cup of coffee. Limit the use of caffeine-containing medications, foods, or beverages while taking this product because too much caffeine may cause nervousness, irritability, sleeplessness, and, occasionally, rapid heartbeat.

Do not use

- in children under 12 years of age
- as substitute for sleep

Stop use and ask a doctor if fatigue or drowsiness persists or continues to recur

PREGNANCY OR BREAST FEEDING

If pregnant or breast-feeding, ask a health professional before use.

Keep out of reach of children. In case of overdose, get medical help or contact a Poison Control Center right away.

Directions

- adults and children 12 years of age and over:
  take 1/2 to 1 caplet not more often than every 3 to 4 hours

Other information

- store at controlled room temperature of 20-25°C (68-77°F)

Inactive ingredients

carnauba wax, corn starch, FD&C blue #1, hypromellose, microcrystalline cellulose, povidone K30, propylene glycol, stearic acid, sucrose, titanium dioxide

Questions or comments?

call toll-free 1-877-507-6516 (M-F 8AM-4:30PM CST) or www.nodoz.com

PRINCIPAL DISPLAY PANEL - 200 mg Caplet Pouch Carton

Max Strength • Fast Acting

NoDoz®

Alertness Aid

200 mg CAFFEINE EACH

4
CAPLETS
2 POUCHES, 2 CAPLETS PER POUCH

Lil'
Drug Store®